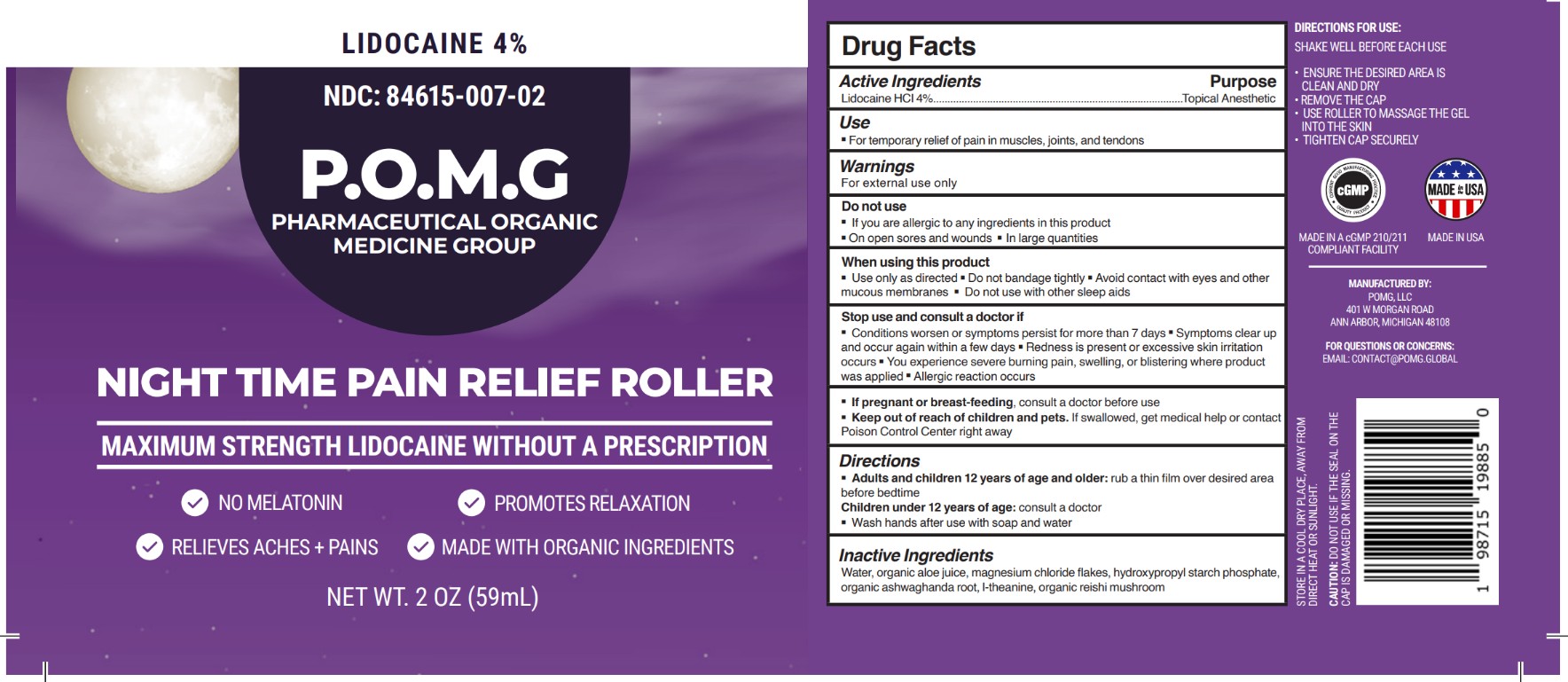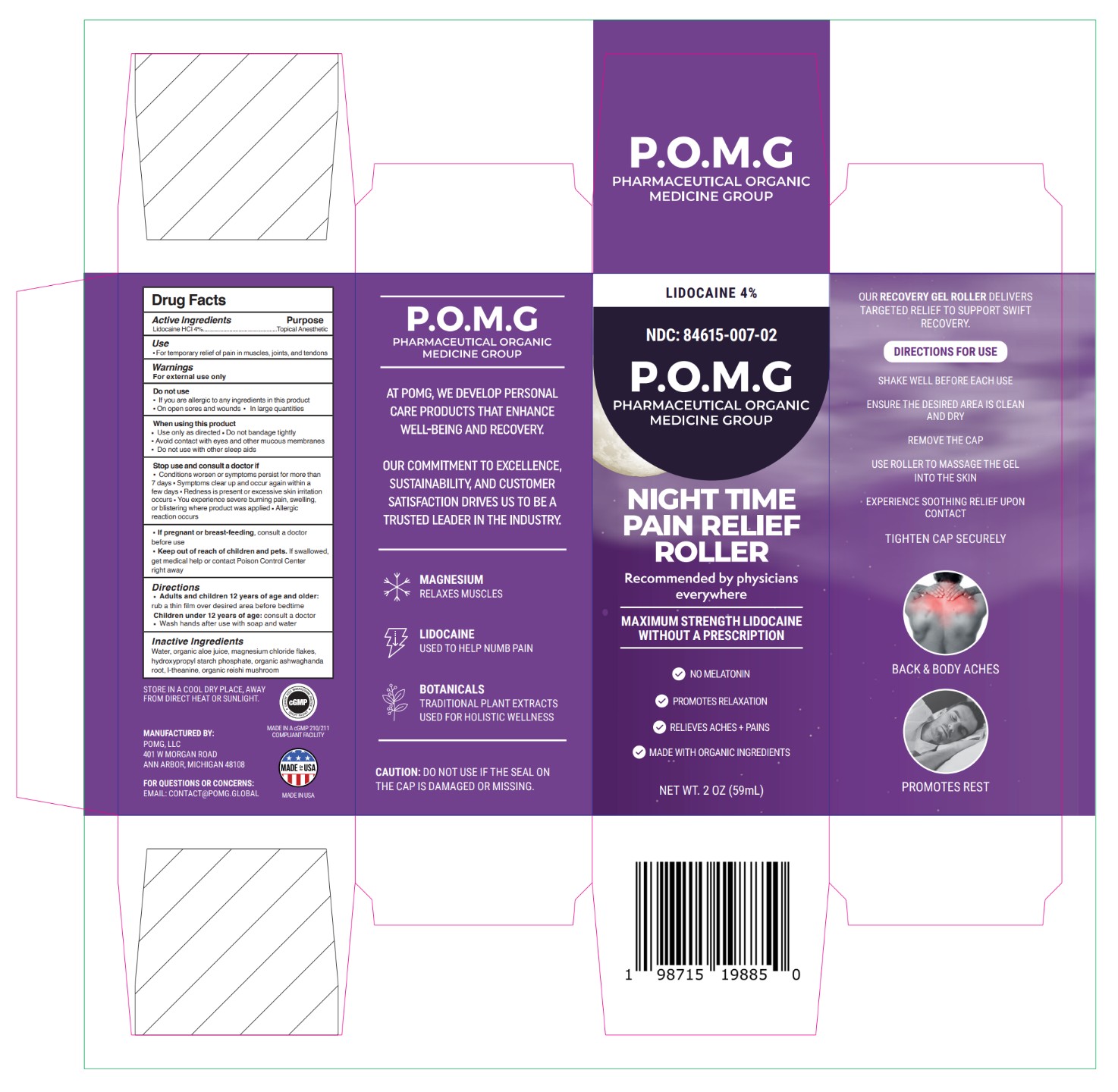 DRUG LABEL: POMG NIGHT TIME PAIN RELIEF ROLLER
NDC: 84615-007 | Form: GEL
Manufacturer: POMG LLC
Category: otc | Type: HUMAN OTC DRUG LABEL
Date: 20251202

ACTIVE INGREDIENTS: LIDOCAINE HYDROCHLORIDE 40 mg/1 mL
INACTIVE INGREDIENTS: ALOE BARBADENSIS LEAF; MAGNESIUM CHLORIDE; WITHANIA SOMNIFERA ROOT; THEANINE; WATER; HYDROXYPROPYL STARCH; REISHI

POMG NIGHT TIME PAIN RELIEF ROLLER

Active Ingredients

Lidocaine HCl 4%

Purpose

Lidocaine HCl 4% ……….…Topical Anesthetic

Use

• For temporary relief of pain in muscles, joints, and tendons

Warnings

For external use only

Do not use

• If you are allergic to any ingredients in this product

• On open sores and wounds

• In large quantities

When using this product

• Use only as directed

• Do not bandage tightly

• Avoid contact with eyes and other mucous membranes

• Do not expose the area to external heat or direct sunlight

Stop use and consult a doctor if

• Conditions worsen or symptoms persist for more than 7 days

• Symptoms clear up and occur again within a few days

• Redness is present or excessive skin irritation occurs

• You experience severe burning pain, swelling, or blistering where product was applied

• Allergic reaction occurs

PREGNANCY OR BREAST FEEDING

• If pregnant or breast-feeding, consult a doctor before use

• Keep out of reach of children and pets. If swallowed, get medical help or contact Poison Control Center right away

Directions

• Adults and children 12 years of age and older: rub a thin film over desired area before bedtime

• Children under 12 years of age: consult a doctor

• Wash hands after use with soap and water

Inactive Ingredients

Water, organic aloe juice, magnesium chloride flakes, hydroxypropyl starch phosphate, organic ashwaghanda root, l-theanine, organic reishi mushroom

PACKAGE LABEL

Lidocaine 4%

NDC: 84615-007-02

P.O.M.G.

Pharmaceutical Organic Medicine Group

Night Time Pain Relief Roller

Maximum Strength Lidocaine Without a Prescription

No Melatonin

Promotes Relaxation

Relieves Aches & Pains

Made with Organic Ingredients

Net Wt. 2 Oz (59mL)